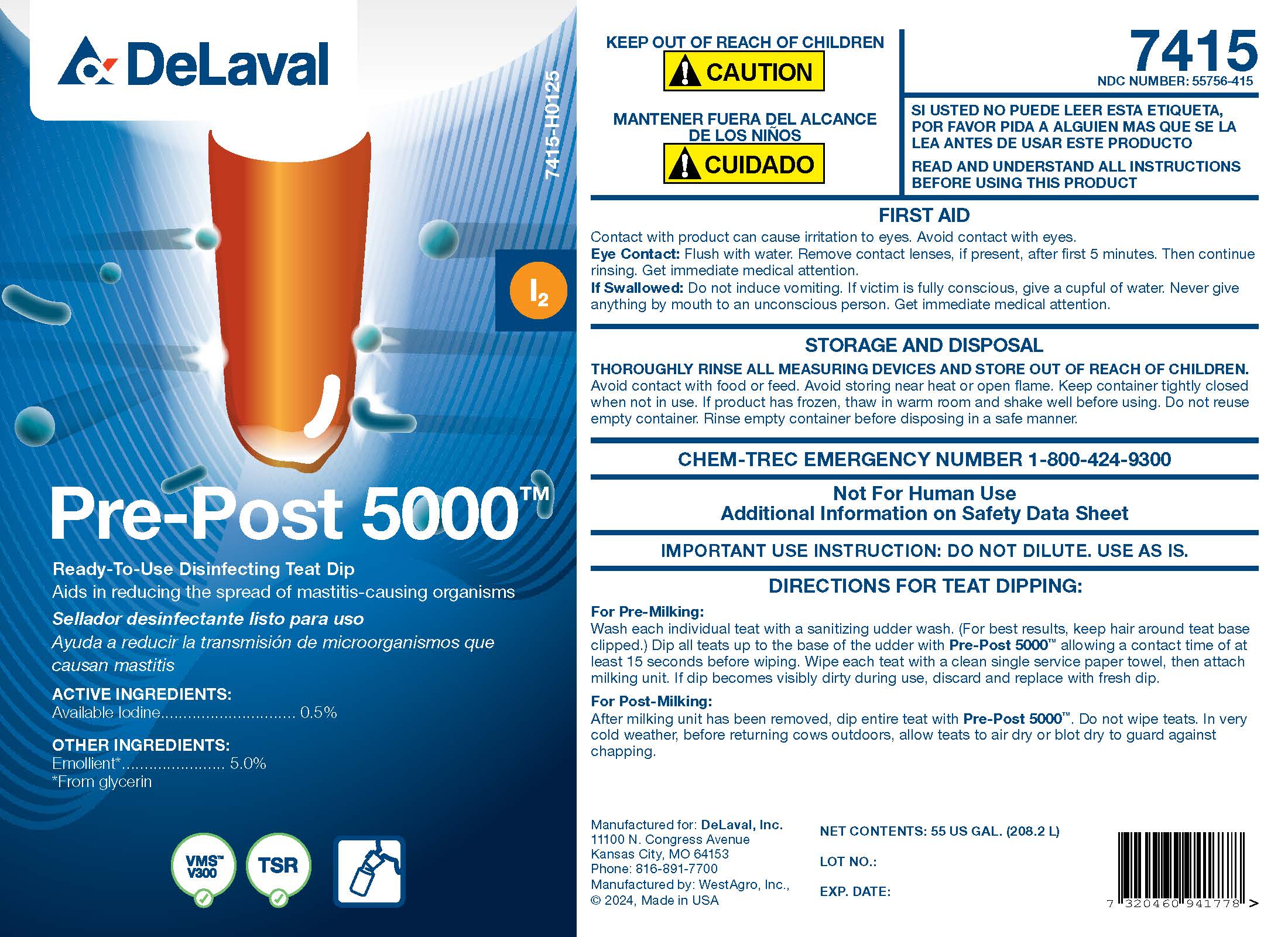 DRUG LABEL: Pre-Post 5000
NDC: 55756-415 | Form: SOLUTION
Manufacturer: DeLaval, Inc.
Category: animal | Type: OTC ANIMAL DRUG LABEL
Date: 20250306

ACTIVE INGREDIENTS: IODINE 5.1 g/1 L

DeLaval Pre-Post 5000™

PURPOSE

Ready-To-Use Disinfecting Teat Dip

Aids in reducing the spread of mastitis-causing organisms

ACTIVE INGREDIENTS:

Available Iodine ............................ 0.5%

OTHER INGREDIENTS:

Emollient* ......................... 5.0%

*From glycerin

KEEP OUT OF REACH OF CHILDREN

! CAUTION

WARNINGS AND PRECAUTIONS

READ AND UNDERSTAND ALL INSTRUCTIONS BEFORE USING THIS PRODUCT

FIRST AID

Contact with product can cause irritation to eyes. Avoid contact with eyes.

Eye Contact: Flush with water. Remove contact lenses, if present, after first 5 minutes. Then continue rinsing. Get immediate medical attention.

If Swallowed: Do not induce vomiting. If victim is fully conscious, give a cupful of water. Never give anything by mouth to an unconscious person. Get immediate medical attention.

STORAGE AND DISPOSAL

THOROUGHLY RINSE ALL MEASURING DEVICES AND STORE OUT OF REACH OF CHILDREN. Avoid contact with food or feed. Avoid storing near heat or open flame. Keep container tightly closed when not in use. If product has frozen, thaw in warm room and shake well before using. Do not reuse empty container. Rinse empty container before disposing in a safe manner.

CHEM-TREC EMERGENCY NUMBER 1-800-424-9300

WARNINGS

Not For Human Use

Additional Information on Safety Data Sheet

INDICATIONS AND USAGE

IMPORTANT USE INSTRUCTION: DO NOT DILUTE. USE AS IS.

DIRECTIONS FOR TEAT DIPPING:

For Pre-Milking:

Wash each individual teat with a sanitizing udder wash. (For best results, keep hair around teat base clipped.) Dip all teats up to the base of the udder with Pre-Post 5000™ allowing a contact time of at least 15 seconds before wiping. Wipe each teat with a clean single service paper towel, then attach milking unit. If dip becomes visibly dirty during use, discard and replace with fresh dip.

For Post-Milking:

After milking unit has been removed, dip entire teat with Pre-Post 5000™. Do not wipe teats. In very cold weather, before returning cows outdoors, allow teats to air dry or blot dry to guard against chapping.

NET CONTENTS: US GAL. (L)

LOT NO.:

EXP. DATE:

PACKAGE LABEL

Add image transcription here...